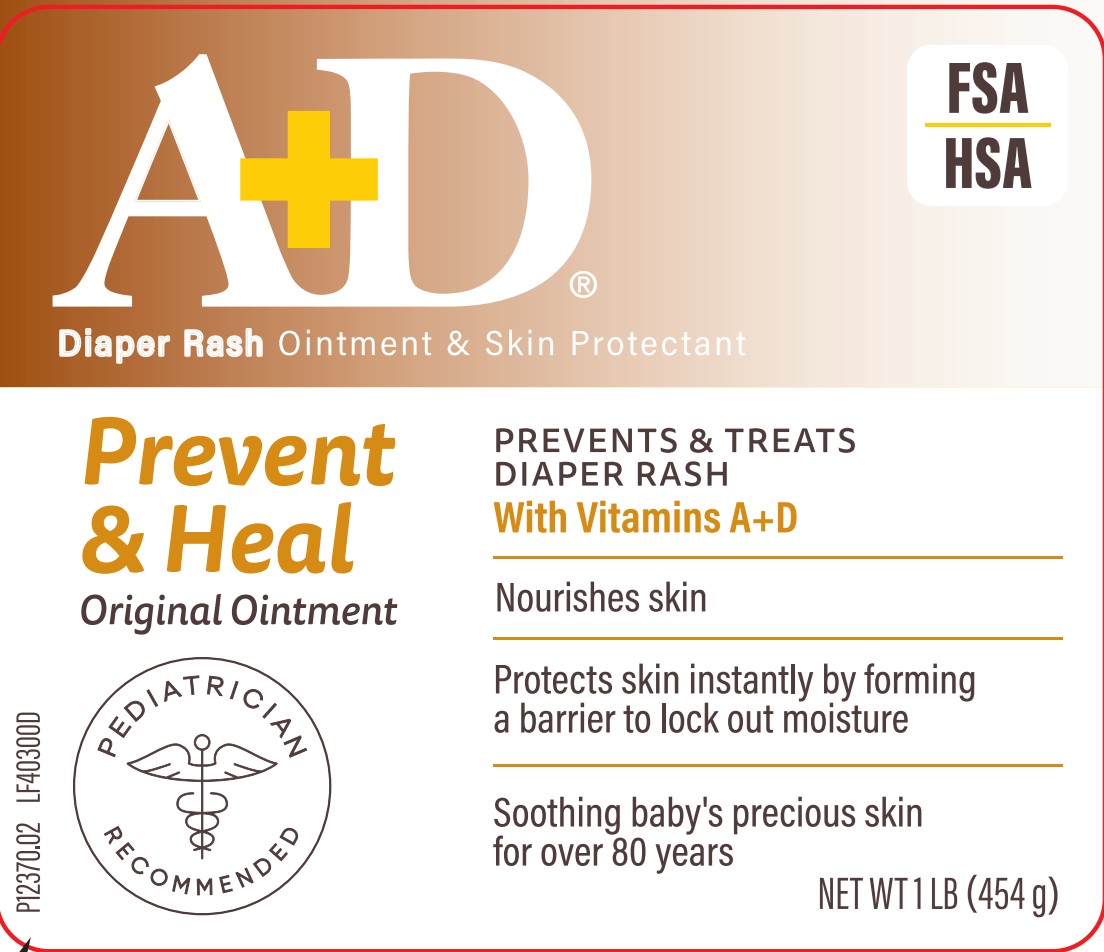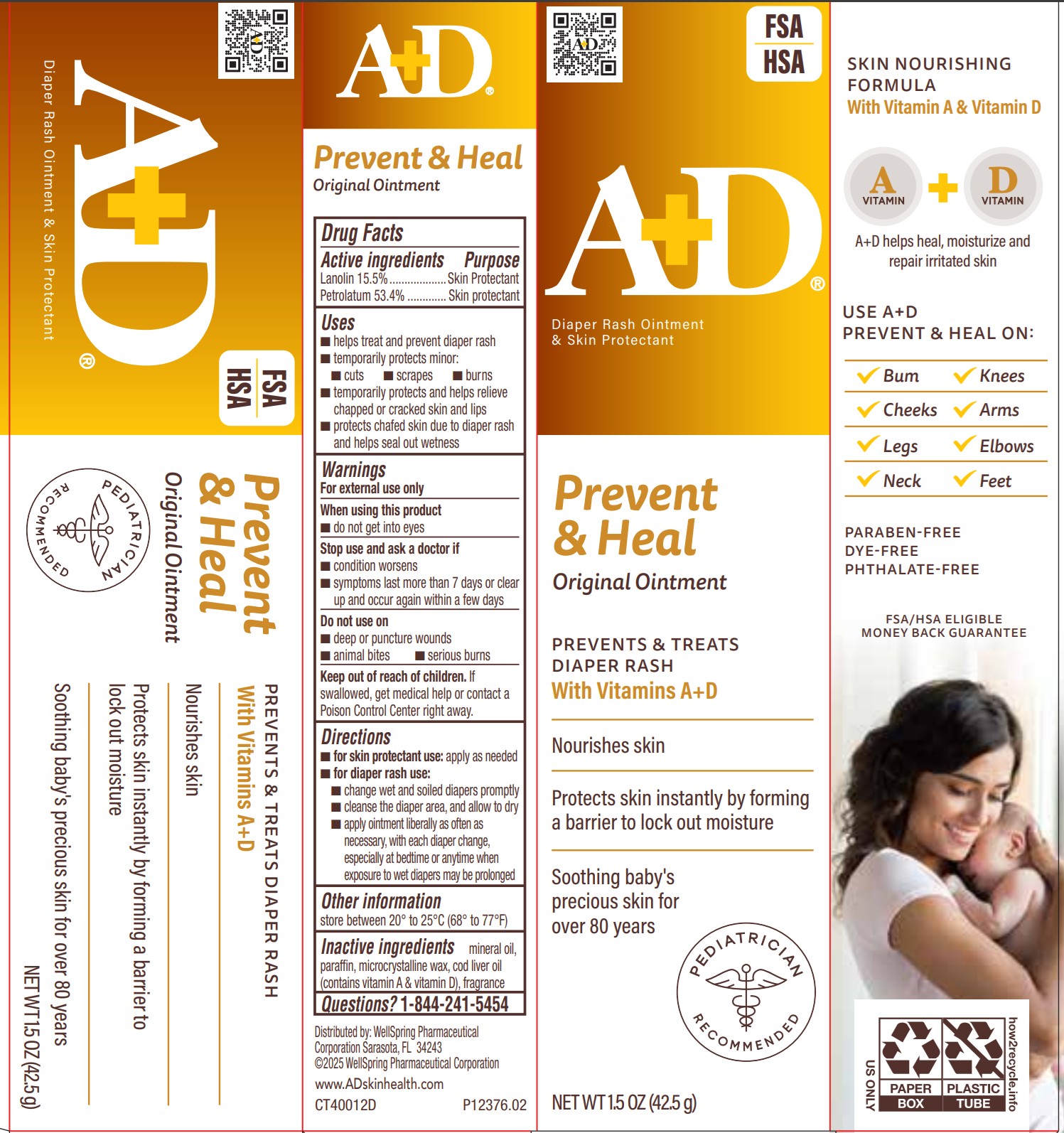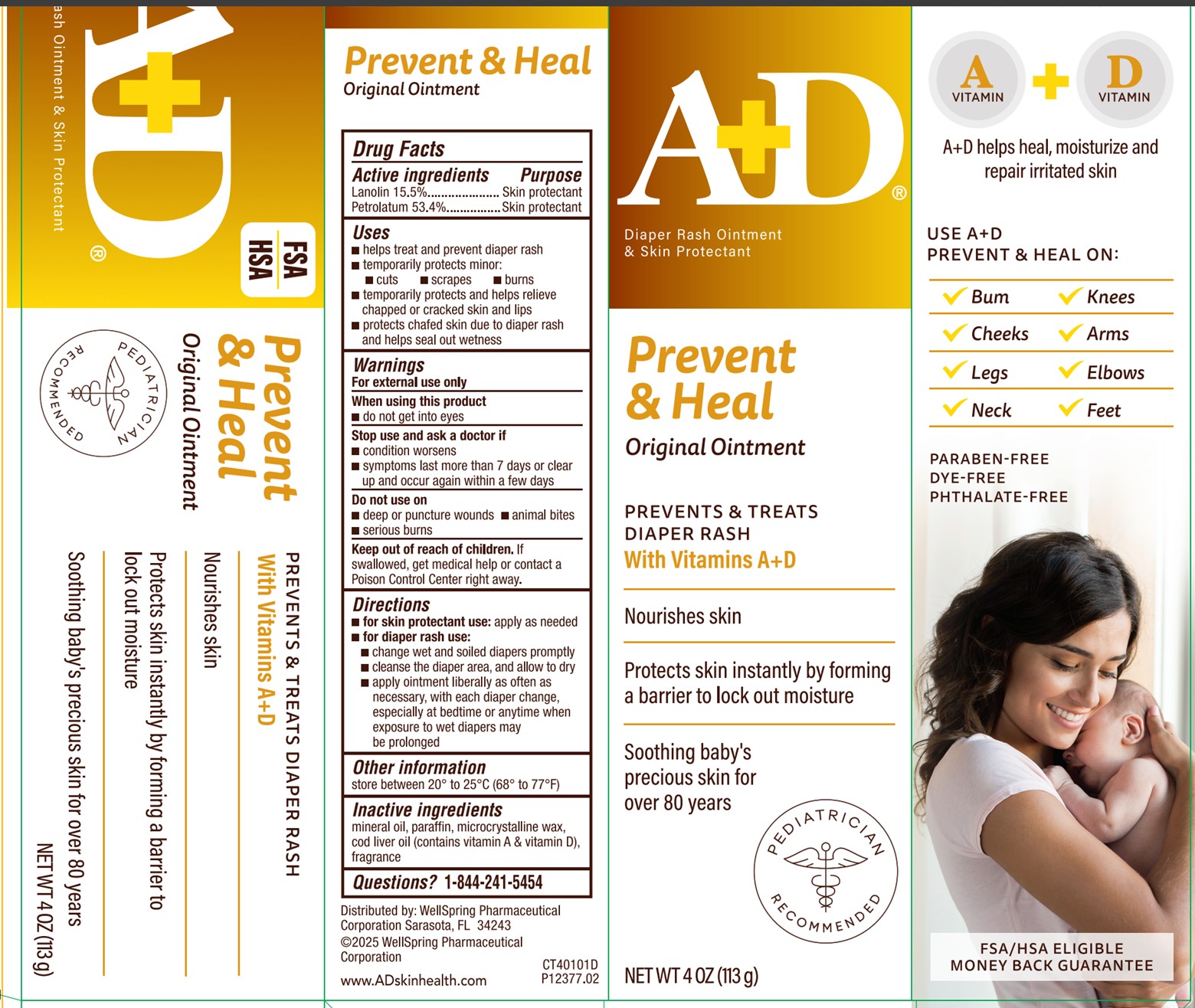 DRUG LABEL: AD PREVENT Original
NDC: 65197-401 | Form: OINTMENT
Manufacturer: WellSpring Pharmaceutical Corporation
Category: otc | Type: HUMAN OTC DRUG LABEL
Date: 20250724

ACTIVE INGREDIENTS: LANOLIN 15.5 g/100 g; PETROLATUM 53.4 g/100 g
INACTIVE INGREDIENTS: COD LIVER OIL; LIGHT MINERAL OIL; MICROCRYSTALLINE WAX; PARAFFIN

A+D PREVENT Original Ointment Diaper Rash Ointment + Skin Protectant

Active Ingredients

Lanolin 15.5%

Petrolatum 53.4%

Purpose

Diaper rash ointment

Skin protectant

Uses

- helps treat and prevent diaper rash
- temporarily protects minor:
- cuts
- scrapes
- burns
- temporarily protects and helps relieve chapped or cracked skin and lips
- protects chafed skin due to diaper rash and helps seal out wetness

Warnings

For external use only

When using this product

- do not get into eyes

Stop use and ask a doctor if

- condition worsens
- symptoms last more than 7 days or clear up and occur again within a few days

Do not use on

- deep or puncture wounds
- animal bites
- serious burns

Keep out of reach of children

- If swallowed, get medical help or contact a Poison Control Center right away.

Directions

- for skin protectant use: apply as needed
- for diaper rash use:
  - change wet and soiled diapers promptly
  - cleanse the diaper area, and allow to dry
  - apply ointment liberally as often as
    necessary, with each diaper change,
    especially at bedtime or anytime when
    exposure to wet diapers may
    be prolonged

Other information

store between 20° to 25°C (68° to 77°F)

Inactive ingredients

cod liver oil (contains vitamin A & vitamin D), fragrance, light mineral oil, microcrystalline wax, paraffin

Questions?

1-844-241-5454

Distributed by:

WellSpring Pharmaceutical Corporation
Sarasota, FL 34243

© 2023 WellSpring Pharmaceutical Corporation

www.ADskinhealth.com

PACKAGE LABEL. PRINCIPAL DISPLAY PANEL

A+D PREVENT

Trusted for over 80 years

A+D® provides gentle and effective solutions for baby's precious skin.

A+D PREVENT

Original Ointment Diaper Rash Ointment + Skin Protectant

Helps prevent & treat diaper rash

Instantly forms a protective barrier to help seal out wetness

PEDIATRICIAN RECOMMENDED

PARABEN-FREE

DYE-FREE

PHTHALATE-FREE

NET WT 4OZ (113g)

NET WT 1.5OZ (42.5g)

Original 16oz
Original 1.5oz
Original 4oz